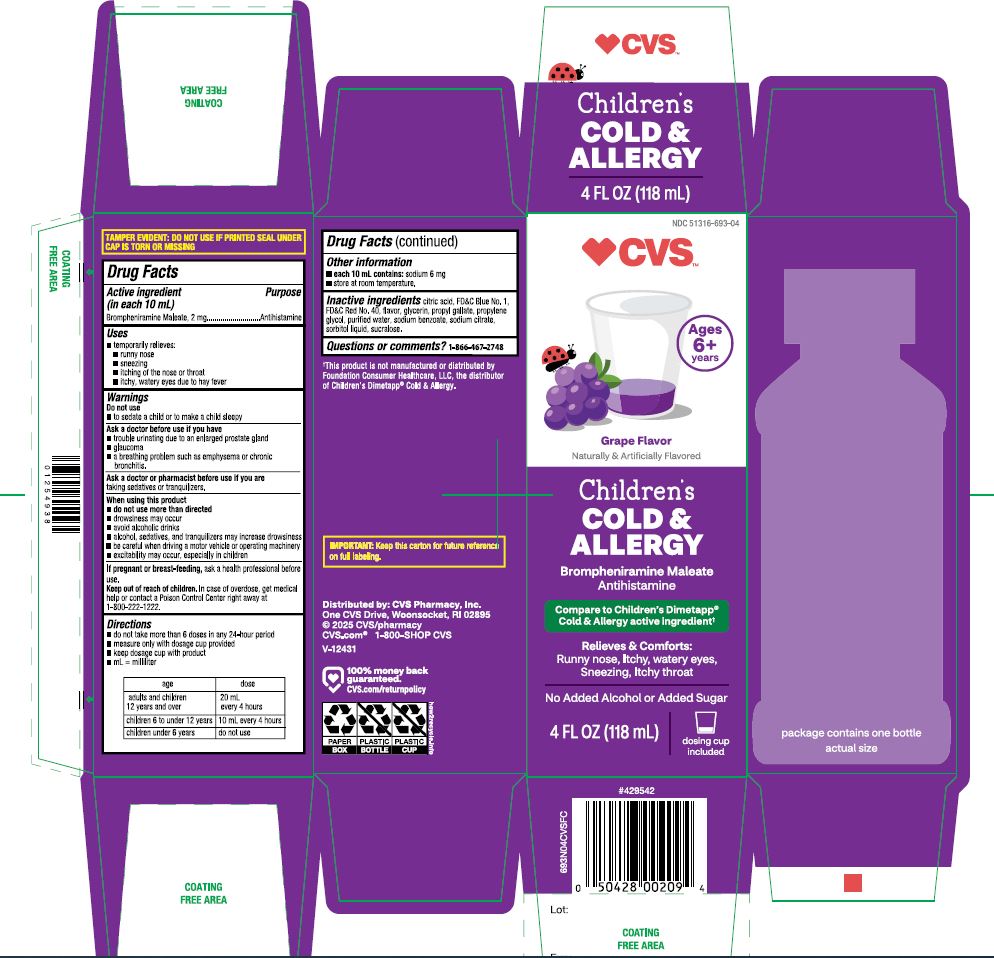 DRUG LABEL: CVS PHARMACY

NDC: 51316-693 | Form: LIQUID
Manufacturer: CVS PHARMACY, INC.
Category: otc | Type: HUMAN OTC DRUG LABEL
Date: 20250603

ACTIVE INGREDIENTS: BROMPHENIRAMINE MALEATE 2 mg/10 mL
INACTIVE INGREDIENTS: ANHYDROUS CITRIC ACID; FD&C BLUE NO. 1; FD&C RED NO. 40; GLYCERIN; PROPYL GALLATE; PROPYLENE GLYCOL; WATER; SODIUM BENZOATE; SODIUM CITRATE, UNSPECIFIED FORM; SORBITOL; SUCRALOSE

CVS Children's Cold & Allergy

Active Ingredients (in each 10 mL)

Brompheniramine maleate, USP 2 mg

Purposes

Antihistamine

Uses

- temporarily relieves:
  - runny nose
  - sneezing
  - itchy, watery eyes due to hay fever
  - itching of the nose or throat

Warnings

Do not use

- to sedate a child or to make a child sleepy

Ask a doctor before use if you have

- trouble urinating due to an enlarged prostate gland
- glaucoma
- a breathing problem such as emphysema, or chronic bronchitis.

Ask a doctor or pharmacist before use if you are

- taking sedatives or tranquilizers

When using this product

- do not use more than directed
- drowsiness may occur
- avoid alcoholic drinks
- alcohol, sedatives, and tranquilizers may increase drowsiness
- be careful when driving a motor vehicle or operating machinery
- excitability may occur, especially in children

If pregnant or breast-feeding,

ask a health professional before use.

Keep out of reach of children.

In case of overdose, get medical help or contact a Poison Control Center right away at 1-800-222-1222.

Directions

- do not take more than 6 doses in any 24-hour period
- measure only with dosage cup provided
- keep dosage cup with product
- ml = milliliter

age | Dose
adults and children 12 years and over | 20 ml every 4 hours
children 6 to under 12 years | 10 ml every 4 hours
children under 6 years | do not use

Other information

- each 10 ml contains:sodium 6 mg
- store at room temperature

Inactive ingredients

citric acid, FD&C Blue No. 1, FD&C Red No. 40, flavor, glycerin, propylene glycol, propyl gallate, purified water, sodium benzoate, sodium citrate, sorbitol liquid, sucralose

Questions or comments?

1-866-467-2748

PRINCIPAL DISPLAY PANEL - 118 ml Bottle Label

Compare to the active ingredients in Children’s Dimetapp® Cold & Allergy*

NDC# 51316-693-04

Children's Cold& Allergy

Brompheniramine Maleate USP (Antihistamine)
Relieves + comforts:

- Runny Nose
- Itchy, Watery Eyes
- Sneezing
- Itchy throat

For Ages 6 Years and Over

Grape Flavor

Naturally and Artificially Flavored

No Added Alcohol

No Added Sugar

4 FL OZ (118 ml)

IMPORTANT:Keep this carton for future reference on full labeling.

Distributed by:

*This product is not manufactured or distributed by Foundation Consumer Healthcare, LLC, the distributor of Children’s Dimetapp® Cold & Allergy.